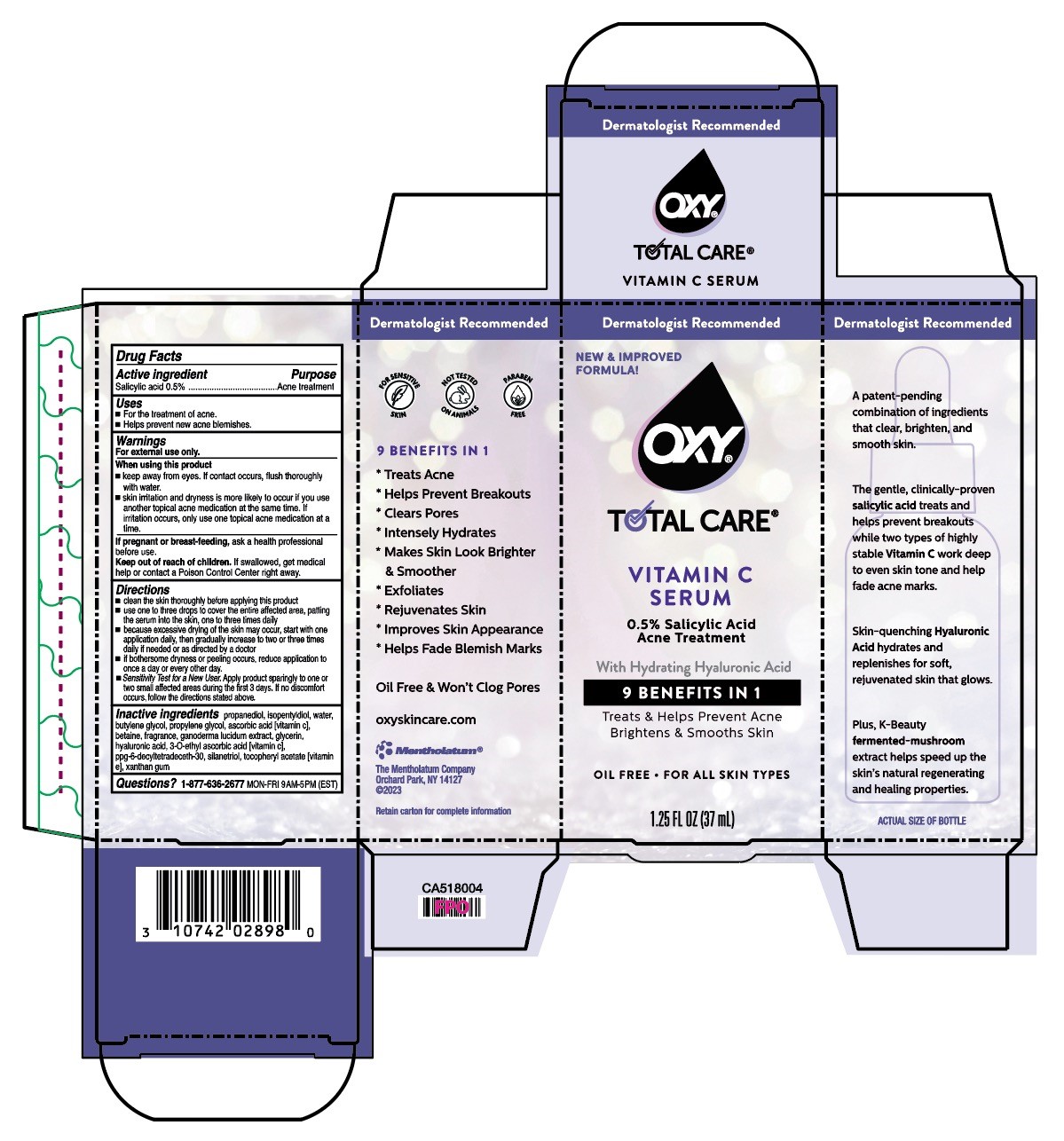 DRUG LABEL: Oxy
NDC: 10742-1315 | Form: SOLUTION
Manufacturer: The Mentholatum Company
Category: otc | Type: HUMAN OTC DRUG LABEL
Date: 20241213

ACTIVE INGREDIENTS: SALICYLIC ACID 5 mg/1 mL
INACTIVE INGREDIENTS: WATER; DIETHYLENE GLYCOL MONOETHYL ETHER; BUTYLENE GLYCOL; GLYCERIN; DISTEARETH-100 ISOPHORONE DIISOCYANATE; 3-O-ETHYL ASCORBIC ACID; PEG-8 DIMETHICONE; PEG-8 RICINOLEATE; ANHYDROUS CITRIC ACID; REISHI; HYALURONIC ACID; POTASSIUM SORBATE; PROPANEDIOL; SILANETRIOL; SODIUM BENZOATE; XANTHAN GUM

Drug Facts - OXY Total Care Vitamin C Serum

Active ingredient

Salicylic acid 0.5%

Purpose

Salicylic acid – Acne treatment

Keep Out of Reach of Children

If swallowed, get medical help or contact a Poison Control Center right away.

Uses

- For the treatment of acne.
- Helps prevent new acne blemishes.

Warnings

For external use only.

When using this product

- keep away from eyes. If contact occurs, flush thoroughly with water.
- skin irritation and dryness is more likely to occur if you use another topical acne medication at the same time. If irritation occurs, only use one topical acne medication at a time.

If pregnant or breast-feeding, ask a health professional before use.

Directions

- clean the skin thoroughly before applying this product
- use one to three drops to cover the entire affected area with a thin layer one to three times daily
- because excessive drying of the skin may occur, start with one application daily, then gradually increase to two or three times daily if needed or as directed by a doctor
- if bothersome dryness or peeling occurs, reduce application to once a day or every other day.
- Sensitivity Test for a New User. Apply product sparingly to one or two small affected areas during the first 3 days. If no discomfort occurs, follow the directions stated above.

Inactive Ingredients

water, ethoxydiglycol, butylene glycol, glycerin, disteareth-100 IPDI, 3-O-ethyl ascorbic acid [vitamin C], PEG-8 dimethicone, PEG-8 ricinoleate, citric acid, fragrance, ganoderma lucidum [mushroom] extract, hyaluronic acid, potassium sorbate, propanediol, silanetriol, sodium benzoate, xanthan gum

Questions?1-877-636-2677

MON-FRI 9AM-5PM (EST)

Package/Label Principal Display Panel

OXY Total Care Vitamin Serum